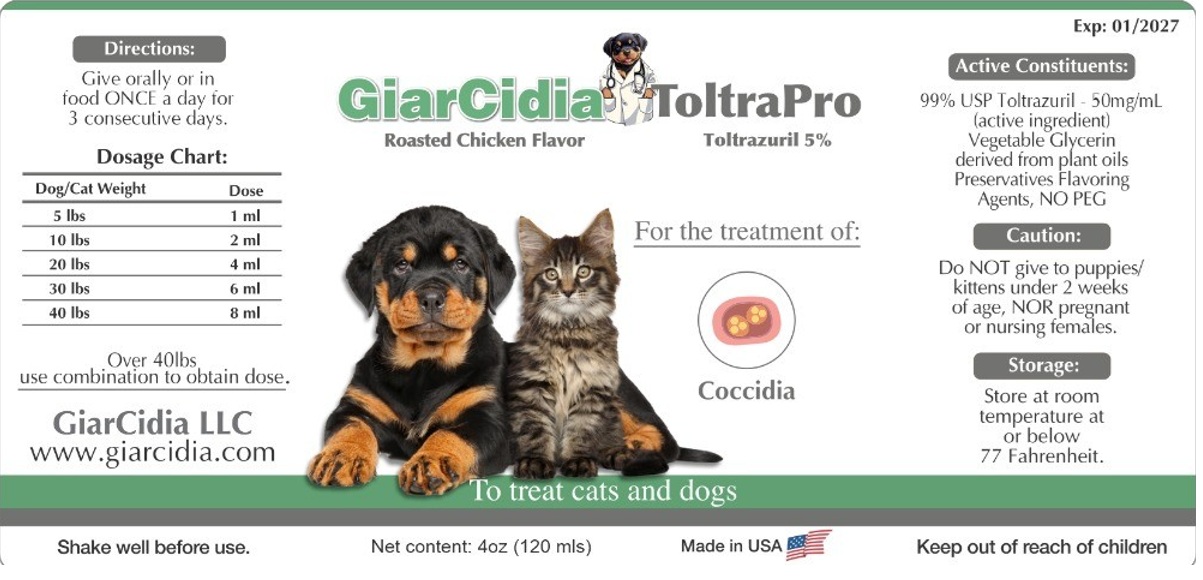 DRUG LABEL: GiarCidia ToltraPro
NDC: 86218-995 | Form: LIQUID
Manufacturer: GiarCidia LLC
Category: animal | Type: OTC ANIMAL DRUG LABEL
Date: 20250616

ACTIVE INGREDIENTS: TOLTRAZURIL 50 mg/1 mL
INACTIVE INGREDIENTS: GLYCERIN; POTASSIUM SORBATE; SODIUM BENZOATE

GiarCidia ToltraPro

Active Constituents:

99% USP Toltrazuril - 50mg/mL (active ingredient)

INACTIVE INGREDIENT

Vegetable Glycerin derived from plant oils Preservatives Flavoring Agents, NO PEG

Caution:

Do NOT give to puppies/ kittens under 2 weeks of age, NOR pregnant or nursing females.

Keep out of reach of children

Storage:

Store at room temperature at or below 77 Fahrenheit.

Directions:

Give orally or in food ONCE a day for 3 consecutive days.

Dosage Chart:
Dog/Cat Weight | Dose
5 lbs | 1 ml
10 lbs | 2 ml
20 lbs | 4 ml
30 lbs | 6 ml
40 lbs | 8 ml
Over 40lbs
use combination to obtain dose.

Shake well before use.

Roasted Chicken Flavor

Toltrazuril 5%

To treat cats and dogs

For the treatment of:

Coccidia

Made in USA

GiarCidia LLC
www.giarcidia.com